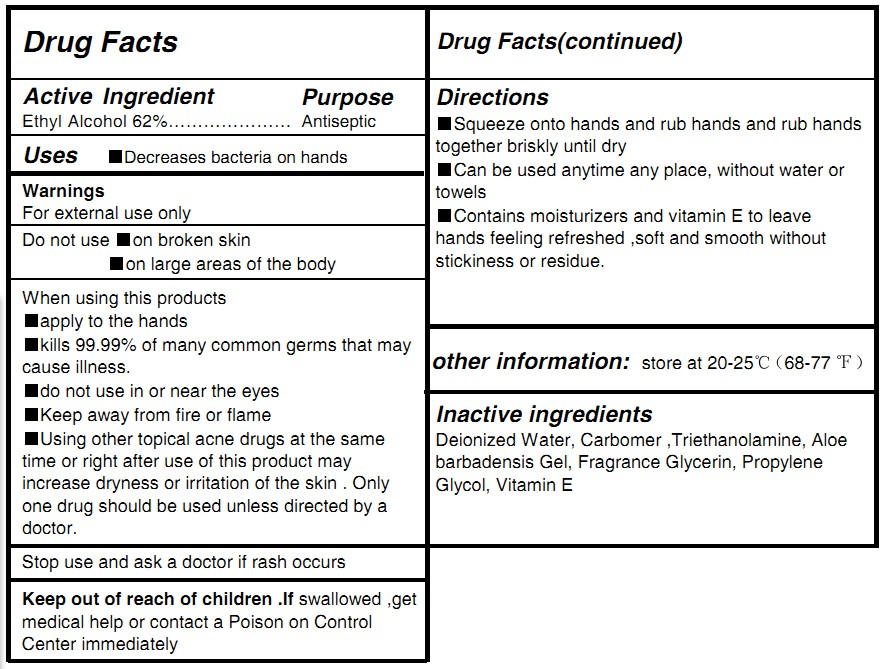 DRUG LABEL: HAND SANITIZER
NDC: 71011-001 | Form: GEL
Manufacturer: NingBo Huize Commodity Co.,Ltd.
Category: otc | Type: HUMAN OTC DRUG LABEL
Date: 20180106

ACTIVE INGREDIENTS: ALCOHOL 62 mL/100 mL
INACTIVE INGREDIENTS: WATER; GLYCERIN; TRIETHANOLAMINE DIOLEATE; 24-HOMO-1,25-DIHYDROXYVITAMIN D3; ALOE VERA LEAF; CARBOMER 934; PROPYLENE GLYCOL DIACETATE

HAND SANITIZER

Active Ingredient

Ethyl Alcohol 62%

Purpose

Antiseptic

Use

Decreases bacteria on hands

Warning

for external use only

Do not use

on broken skin

on large areas of the body

Keep out of reach of children

If swallowed ,get medical help or contact a Poison on Control Center immediately

Directions

Squeeze ont oh ands and rub hands and rub hands together briskly until dry

Can be used anytime any place, without water or towels

Contains moisturizers and vitamin E to leave hands feeling refreshed ,soft and smooth without stickiness or residue.

INACTIVE INGREDIENT

Deionized Water, Carbomer ,Triethanolamine, Aloe barbadensis Gel, Fragrance Glycerin,
Propylene Glycol,Vitamin E